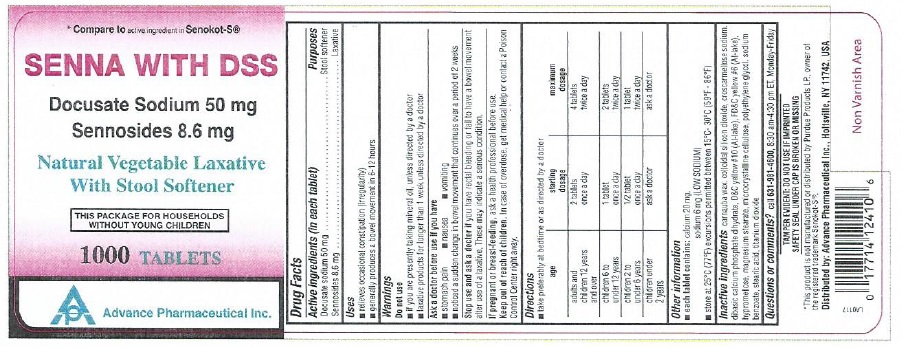 DRUG LABEL: SENNA-S
NDC: 17714-124 | Form: TABLET
Manufacturer: Advance Pharmaceutical Inc.
Category: otc | Type: HUMAN OTC DRUG LABEL
Date: 20171030

ACTIVE INGREDIENTS: SENNOSIDES 8.6 mg/1 1; DOCUSATE SODIUM 50 mg/1 1
INACTIVE INGREDIENTS: CARNAUBA WAX; CROSCARMELLOSE SODIUM; SILICON DIOXIDE; CALCIUM PHOSPHATE, DIBASIC, DIHYDRATE; D&C YELLOW NO. 10; FD&C YELLOW NO. 6; HYPROMELLOSES; CELLULOSE, MICROCRYSTALLINE; MAGNESIUM STEARATE; POLYETHYLENE GLYCOL 1000; SODIUM BENZOATE; STEARIC ACID; TITANIUM DIOXIDE

Senna-S - Senna and Docusate Sodium Tablets, 8.6 mg & 50 mg

Drug Facts

ACTIVE INGREDIENT

Senna Tablets- 8.6 mg

Docusate Sodium- 50 mg

PURPOSE

Senna Tablets- 8.6 mg ..........Laxative

Docusate Sodium- 50 mg........Stool softner

Uses

- relieves occasional constipation (irregularity)
- generally produces bowel movement in 6-12 hours

Warnings

Do not use

- if you are now taking mineral oil, unless directed by a doctor
- laxative products for longer than 1 week unless directed by a doctor

Ask a doctor before use if you have

- stomach pain
- nausea
- vomiting
- noticed a sudden change in bowel habits that lasts over 2 weeks

Stop use and ask a doctor if

you have rectal bleeding or fail to have a bowel movement after use of a laxative. These may indicate a serious condition.

PREGNANCY OR BREAST FEEDING

If pregnant or breast-feeding, ask a health professional before use.

Keep out of reach of children.

In case of overdose, get medical help or contact a Poison Control Center right away.

Directions

take preferably at bedtime or as directed by a doctor

- adults and children 12 years of age or older - starting dosage: 2 tablets once a day, maximum dosage: 4 tablets twice a day
- children 6 to under 12 years - starting dosage: 1 tablet once a day, maximum dosage: 2 tablets twice a day
- children 2 to under 6 years - starting dosage: 1/2 tablet once a day, maximum dosage: 1 tablet twice a day
- children under 2 years - starting dosage: ask a doctor, maximum dosage: ask a doctor

Other information

- each tablet contains: calcium 21 mg
- each tablet contains: sodium 3 mg VERY LOW SODIUM
- store at 25ºC (77ºF); excursions permitted between 15°-30°C (59°-86°F)
- read all product information before using
- TAMPER EVIDENT: DO NOT USE IF IMPRINTED SAFETY SEAL UNDER CAP IS BROKEN OR MISSING

Inactive ingredients

carnuba wax, croscarmellose sodium, colloidal silicon dioxide, dicalcium phosphate, D&C Yellow # 10, FD&C Yellow # 6, hypromellose, microcrystalline cellulose, magnesium stearate, polyethylene glycol, stearic acid, titanium dioxide

Questions or comments?

call 631-981-4600, 8.30 am-4.30 pm ET, Monday - Friday
TAMPER EVIDENT: DO NOT USE IF IMPRINTED SAFETY SEAL UNDER CAP IS BROKEN OR MISSING

PRINCIPAL DISPLAY PANEL

NDC- 17714-124-10

Senna and Docusate Sodium Tablets, 8.6 mg and 50 mg